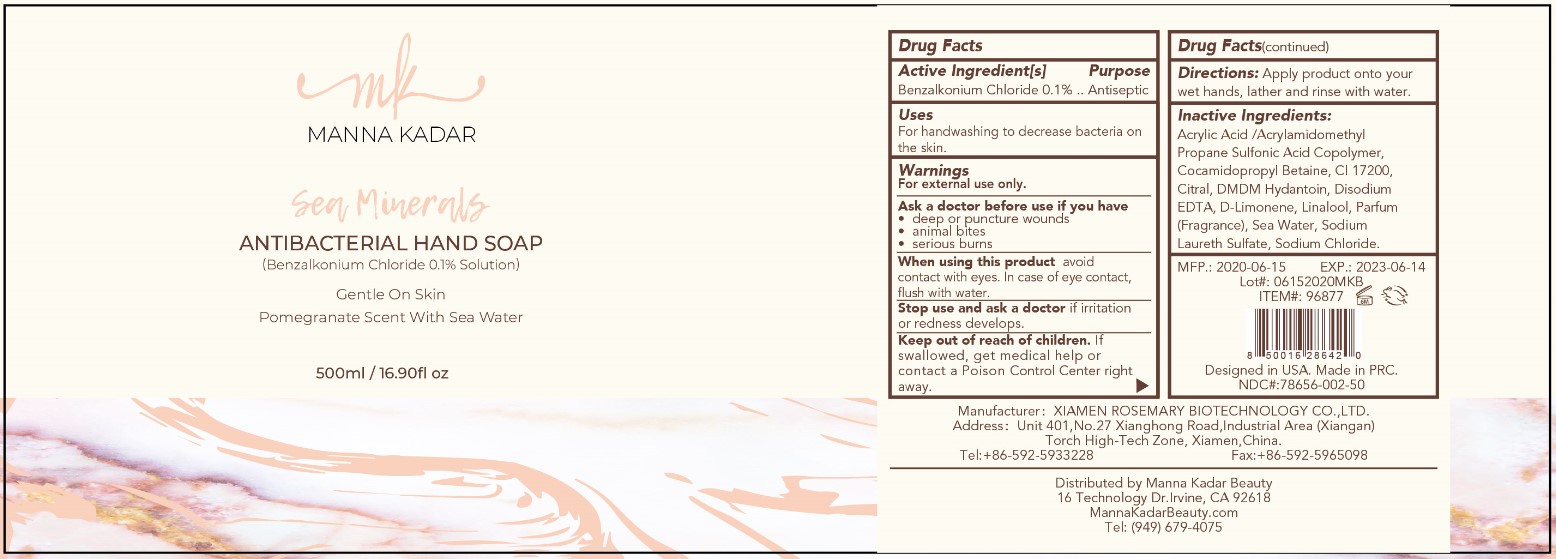 DRUG LABEL: Sea Minerals Antibacterial
NDC: 78656-002 | Form: SOLUTION
Manufacturer: Manna Kadar Beauty Inc.
Category: otc | Type: HUMAN OTC DRUG LABEL
Date: 20201119

ACTIVE INGREDIENTS: BENZALKONIUM CHLORIDE 0.1 g/100 mL
INACTIVE INGREDIENTS: EDETATE DISODIUM; DMDM HYDANTOIN; SODIUM LAURETH SULFATE; 2-ACRYLAMIDO-2-METHYL-1-PROPANESULFONIC ACID; COCAMIDOPROPYL BETAINE; WATER; D&C RED NO. 33; CITRAL; LIMONENE, (+)-; LINALOOL, (+/-)-; SODIUM CHLORIDE

Sea Minerals Antibacterial Hand Soap

Active Ingredient(s)

Benzalkonium Chloride 0.1%

Purpose

Antiseptic

Uses

For handwashing to decrease bacteria on the skin.

Warnings

For external use only.

Ask a doctor before use if you have

• deep or puncture wounds

• animal bites

• serious burns

When using this product

avoid contact with eyes. In case of eye contact, flush with water.

Stop use and ask a doctor if

irritation or redness develops.

Keep out of reach of children.

If swallowed, get medical help or contact a Poison Control Center right away.

Directions

Apply product onto your wet hands, lather and rinse with water.

Other information

• Store at 15° to 30°C (59° to 86°F). Avoid freezing and excessive heat above 40°C (104°F)

Inactive Ingredients

Acrylic Acid /Acrylamidomethyl Propane Sulfonic Acid Copolymer, Cocamidopropyl Betaine, CI 17200, Citral, DMDM Hydantoin, Disodium EDTA, D-Limonene, Linalool, Parfum (Fragrance), Sea Water, Sodium Laureth Sulfate, Sodium Chloride.